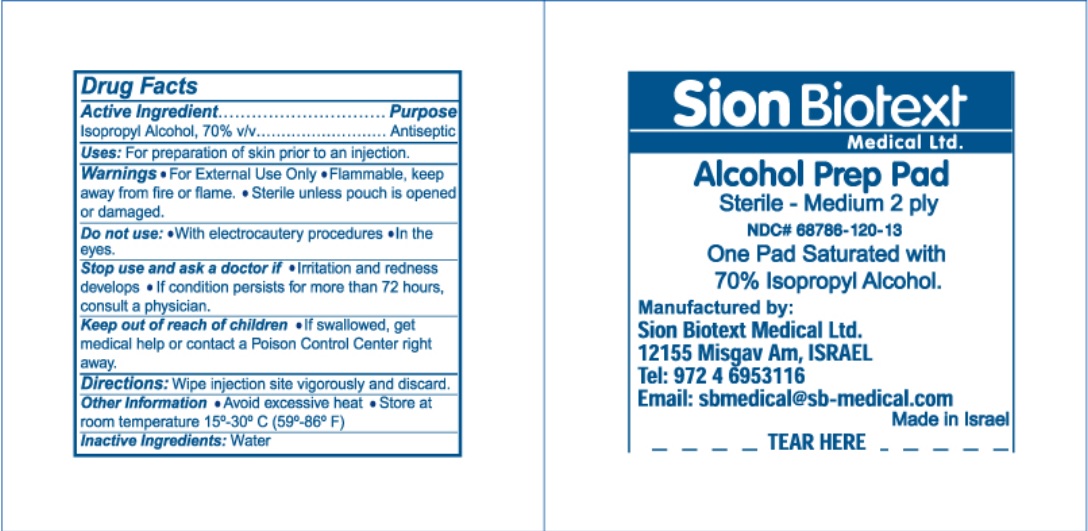 DRUG LABEL: alcohol
NDC: 68786-120 | Form: SWAB
Manufacturer: Sion Biotext Medical Ltd
Category: otc | Type: HUMAN OTC DRUG LABEL
Date: 20240110

ACTIVE INGREDIENTS: ISOPROPYL ALCOHOL 0.7 mL/1 mL
INACTIVE INGREDIENTS: WATER

Sion Sterile Alcohol Prep Pad

Active Ingredient

Isopropyl Alcohol 70% v/v

Purpose

Antiseptic

Uses

For preparation of skin prior to an injection

Warnings:

- For External Use Only
- Flammable, keep away from fire or flame
- Sterile unless pouch is opened or damaged

Do not use:

- With electrocautery procedures
- In the eyes.

Stop use and ask a doctor:

- If irritation and redness develop
- If condition persists for more than 72 hours, consult a physician.

Keep out of reach of children. If swallowed, get medical help or contact a Poison Control Center.

Directions:

- Wipe injection site vigorously and discard.

Other Information

- Avoid excessive heat
- Store at room temperature 15o-30o C (59o-86o F)

Inactive Ingredients

Water

Principal display panel

NDC 68786-120-13

Sion Biotext Medical Ltd.

Alcohol Prep Pad

Sterile- Medium 2 Ply

One pad saturated with 70% Isopropyl Alcohol